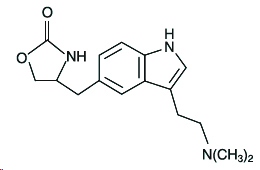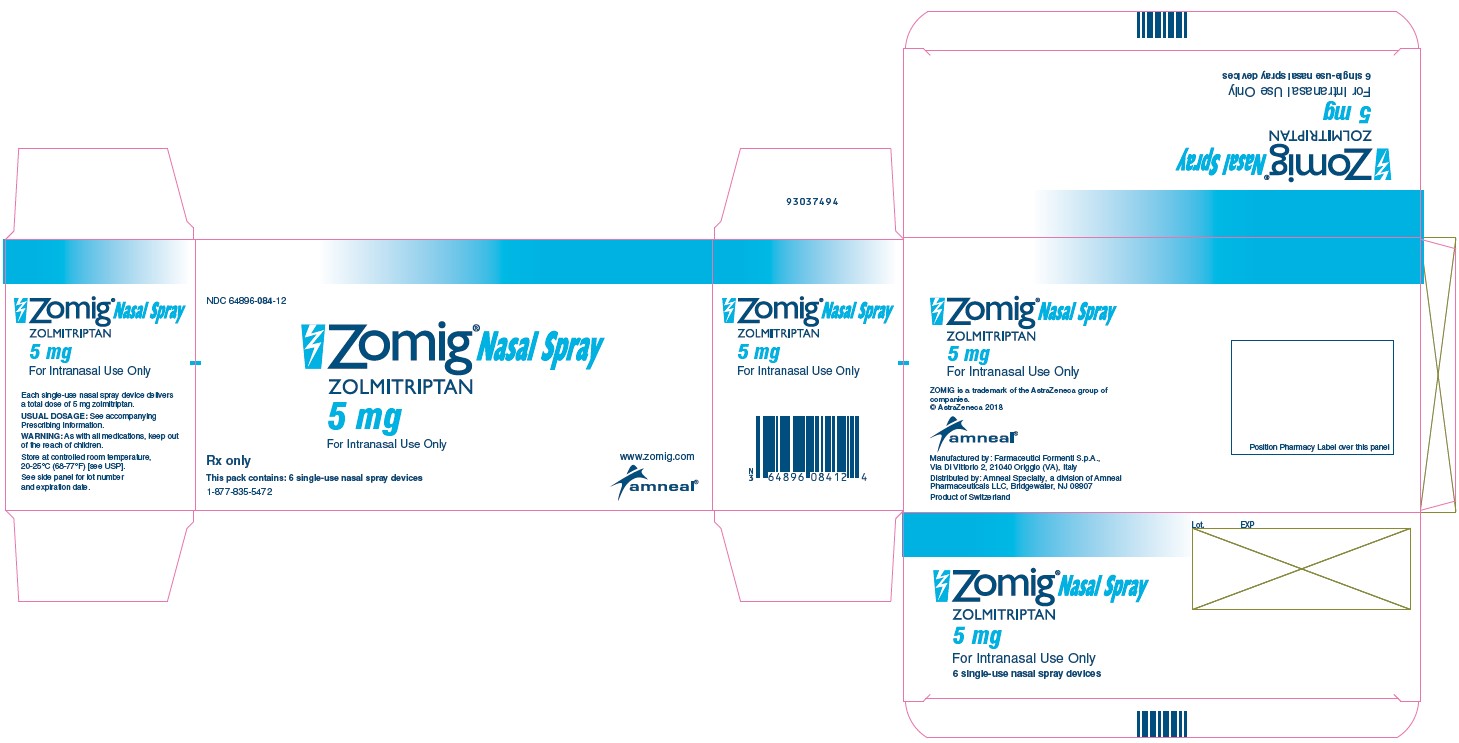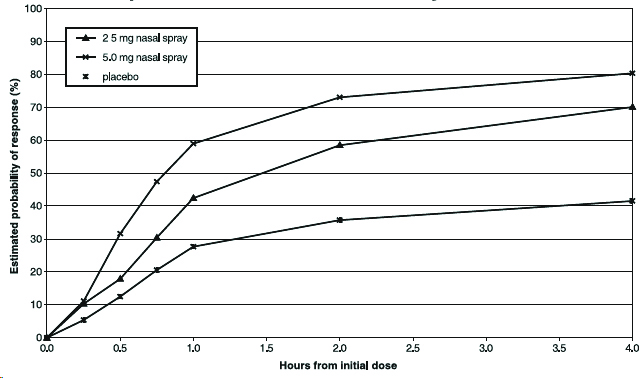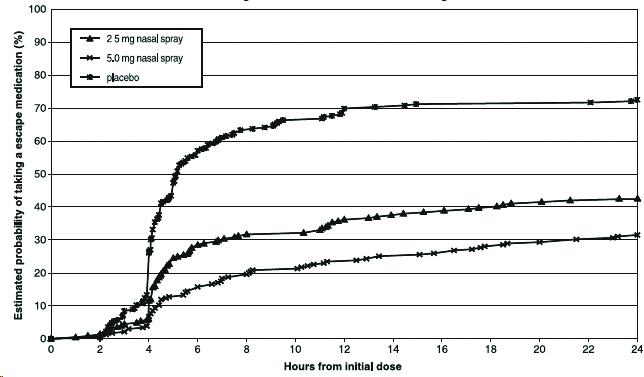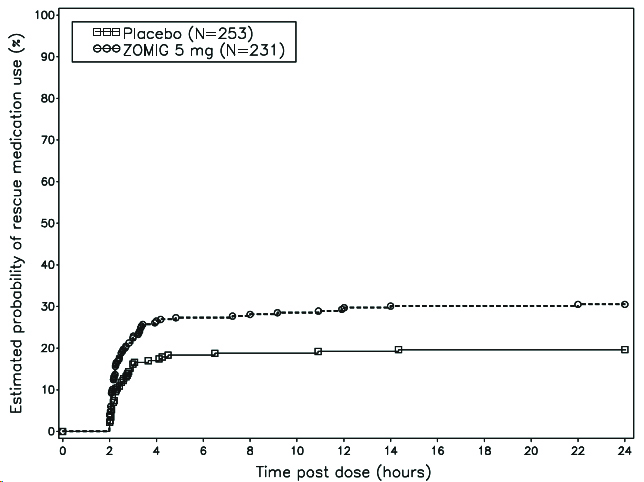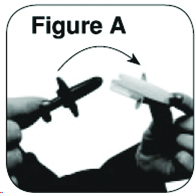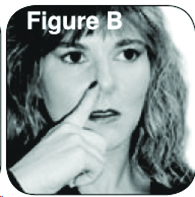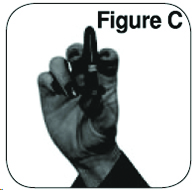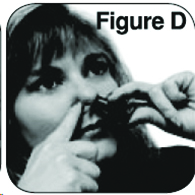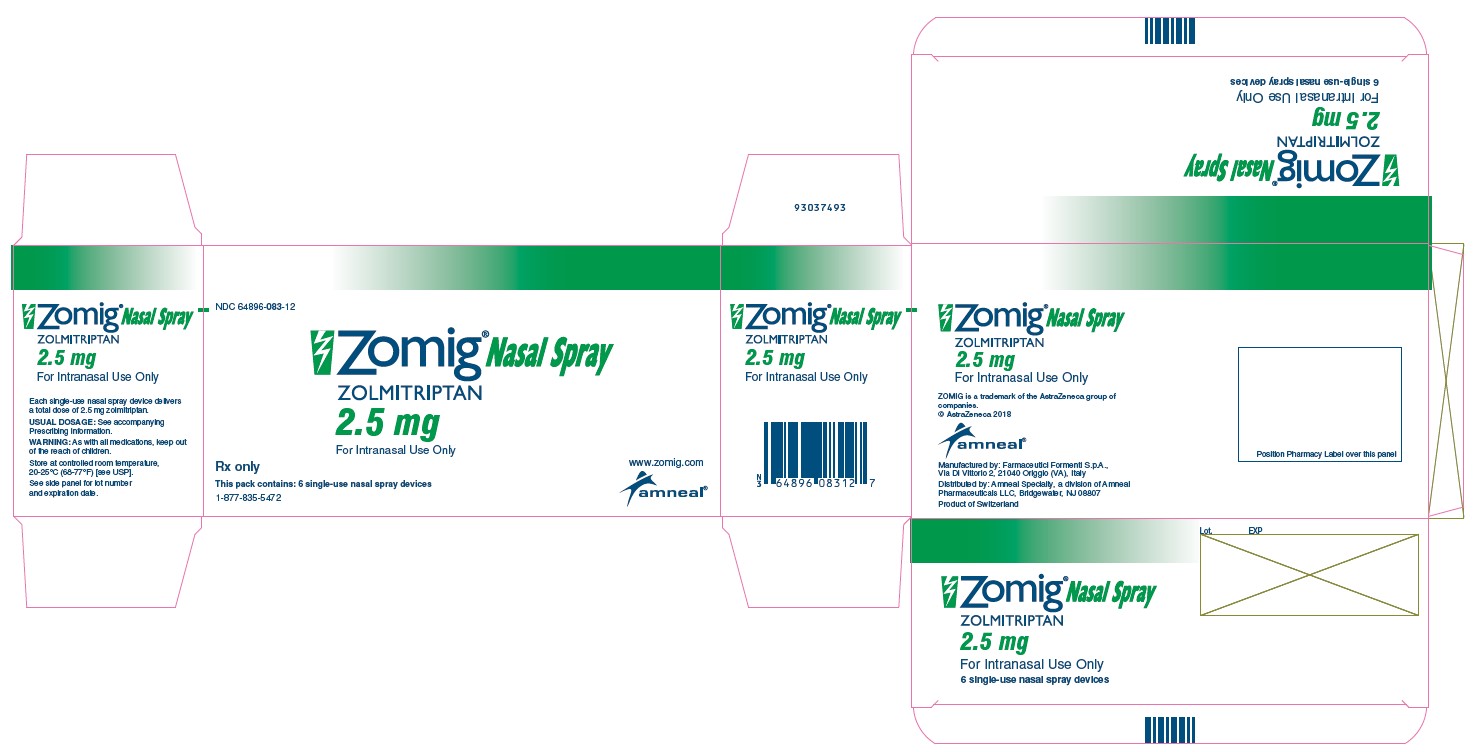 DRUG LABEL: ZOMIG
NDC: 64896-083 | Form: SPRAY, METERED
Manufacturer: Amneal Pharmaceuticals LLC
Category: prescription | Type: HUMAN PRESCRIPTION DRUG LABEL
Date: 20190430

ACTIVE INGREDIENTS: ZOLMITRIPTAN 2.5 mg/1 1
INACTIVE INGREDIENTS: ANHYDROUS CITRIC ACID; NITROGEN; SODIUM PHOSPHATE, DIBASIC; WATER

HIGHLIGHTS OF PRESCRIBING INFORMATION

These highlights do not include all the information needed to use ZOMIG Nasal Spray safely and effectively. See full prescribing information for ZOMIG Nasal Spray.
ZOMIG® (zolmitriptan) nasal spray
Initial U.S. Approval: 1997

1 INDICATIONS AND USAGE

- ZOMIG Nasal Spray is a serotonin (5-HT)1B/1D receptor agonist (triptan) indicated for the acute treatment of migraine with or without aura in adults and pediatric patients 12 years and older (1)

Limitations of Use:

- Use only after a clear diagnosis of migraine has been established (1)
- Not intended for the prophylactic therapy of migraine (1)
- Not indicated for the treatment of cluster headache (1)
- Not recommended in patients with moderate to severe hepatic impairment (1)

2 DOSAGE AND ADMINISTRATION

- Recommended starting dose: 2.5 mg (2.1)
- Maximum single dose: 5 mg (2.1)
- May repeat dose after 2 hours if needed; not to exceed 10 mg in any 24-hour period (2.1)

3 DOSAGE FORMS AND STRENGTHS

Nasal Spray: 2.5 mg and 5 mg (3)

4 CONTRAINDICATIONS

- History of ischemic heart disease or coronary artery vasospasm (4)
- Symptomatic Wolff-Parkinson-White syndrome or other cardiac accessory conduction pathway disorders (4)
- History of stroke, transient ischemic attack, or hemiplegic or basilar migraine (4)
- Peripheral Vascular Disease (4)
- Ischemic bowel disease (4)
- Uncontrolled hypertension (4)
- Recent (within 24 hours) use of another 5-HT1 agonist (e.g., another triptan) or of an ergot-type medication (4)
- MAO-A inhibitor used in past 2 weeks (4)
- Hypersensitivity to ZOMIG (4)

5 WARNINGS AND PRECAUTIONS

- Myocardial Ischemia, Myocardial Infarction, and Prinzmetal's Angina: Perform cardiac evaluation in patients with multiple cardiovascular risk factors (5.1)
- Arrhythmias: Discontinue dosing if occurs (5.2)
- Chest/throat/neck/jaw pain, tightness, pressure, or heaviness: Generally not associated with myocardial ischemia; evaluate for coronary artery disease in patients at high risk (5.3)
- Cerebral hemorrhage, subarachnoid hemorrhage, and stroke: Discontinue dosing if occurs (5.4)
- Gastrointestinal ischemic events, peripheral vasospastic reactions: Discontinue dosing if occurs (5.5)
- Medication Overuse Headache: Detoxification may be necessary (5.6)
- Serotonin syndrome: Discontinue dosing if occurs (5.7, 7.5)
- Increase in blood pressure: very rarely associated with significant events (5.8)

6 ADVERSE REACTIONS

The most common adverse reactions (≥ 5% and > placebo) were:

- Adults: unusual taste, paresthesia, dizziness, and hyperesthesia (6.1)
- Pediatrics: unusual taste (6.1)

To report SUSPECTED ADVERSE REACTIONS, contact Amneal Pharmaceuticals at 1-877-835-5472 or FDA at 1-800-FDA-1088 or www.fda.gov/medwatch.

7 DRUG INTERACTIONS

If co-administered with cimetidine: Maximum single dose of 2.5 mg, not to exceed 5 mg in any 24-hour period. (2.3, 7.4)

8 USE IN SPECIFIC POPULATIONS

Pregnancy: Based on animal data, may cause fetal harm (8.1)

FULL PRESCRIBING INFORMATION

1 INDICATIONS AND USAGE

ZOMIG Nasal Spray is indicated for the acute treatment of migraine with or without aura in adults and pediatric patients 12 years of age and older.

Limitations of Use

- Only use ZOMIG if a clear diagnosis of migraine has been established. If a patient has no response to ZOMIG treatment for the first migraine attack, reconsider the diagnosis of migraine before ZOMIG is administered to treat any subsequent attacks.
- ZOMIG is not indicated for the prevention of migraine attacks.
- Safety and effectiveness of ZOMIG have not been established for cluster headache.
- Not recommended in patients with moderate or severe hepatic impairment [see Dosage and Administration (2.2)].

2 DOSAGE AND ADMINISTRATION

2.1 Dosing Information

The recommended starting dose for ZOMIG nasal spray in adult and pediatric patients 12 years of age and older is 2.5 mg. As the individual response to ZOMIG nasal spray may vary, the dose should be adjusted on an individual basis. The maximum recommended single dose of ZOMIG is 5 mg.

If the migraine has not resolved by 2 hours after taking ZOMIG, or returns after a transient improvement, another dose may be administered at least 2 hours after the previous dose.

The maximum daily dose should not exceed 10 mg in any 24-hour period.

The safety of ZOMIG in the treatment of an average of more than four headaches in a 30-day period has not been established.

2.2 Dosing in Patients with Hepatic Impairment

ZOMIG nasal spray is not recommended in patients with moderate to severe hepatic impairment because of increased zolmitriptan blood levels in these patients and elevation of blood pressure in some of these patients. The recommended dosage of ZOMIG nasal spray in patients with mild hepatic impairment is the same as for patients with normal hepatic function [see Dosage and Administration (2.1), Warnings and Precautions (5.8), Use in Specific Populations (8.6) and Clinical Pharmacology (12.3)].

2.3 Dosing in Patients taking Cimetidine

If ZOMIG is co-administered with cimetidine, limit the maximum single dose of ZOMIG to 2.5 mg, not to exceed 5 mg in any 24-hour period [see Drug Interactions (7.4) and Clinical Pharmacology (12.3)].

3 DOSAGE FORMS AND STRENGTHS

Nasal Spray 2.5 mg and 5 mg.

4 CONTRAINDICATIONS

ZOMIG is contraindicated in patients with:

- Ischemic coronary artery disease (angina pectoris, history of myocardial infarction, or documented silent ischemia), other significant underlying cardiovascular disease, or coronary artery vasospasm including Prinzmetal's angina [see Warnings and Precautions (5.1)]
- Wolff-Parkinson-White Syndrome or arrhythmias associated with other cardiac accessory conduction pathway disorders [see Warnings and Precautions (5.2)]
- History of stroke, transient ischemic attack (TIA) or history of hemiplegic or basilar migraine because these patients are at higher risk of stroke [see Warnings and Precautions (5.4)]
- Peripheral vascular disease (PVD) [see Warnings and Precautions (5.5)]
- Ischemic bowel disease [see Warnings and Precautions (5.5)]
- Uncontrolled hypertension [see Warnings and Precautions (5.8)]
- Recent use (i.e., within 24 hours) of another 5-HT1 agonist, ergotamine-containing medication, or ergot-type medication (such as dihydroergotamine or methysergide) [see Drug Interactions (7.1, 7.3)]
- Concurrent administration of an MAO-A inhibitor or recent discontinuation of a MAO-A inhibitor (that is within 2 weeks) [see Drug Interactions (7.2) and Clinical Pharmacology (12.3)]
- Known hypersensitivity to ZOMIG (angioedema and anaphylaxis seen) [see Adverse Reactions (6.2)]

5 WARNINGS AND PRECAUTIONS

5.1 Myocardial Ischemia, Myocardial Infarction, and Prinzmetal's Angina

ZOMIG is contraindicated in patients with ischemic or vasospastic coronary artery disease (CAD). There have been rare reports of serious cardiac adverse reactions, including acute myocardial infarction, occurring within a few hours following administration of ZOMIG. Some of these reactions occurred in patients without known CAD. 5-HT1 agonists including ZOMIG may cause coronary artery vasospasm (Prinzmetal's Angina), even in patients without a history of CAD.

Perform a cardiovascular evaluation in triptan-naïve patients who have multiple cardiovascular risk factors (e.g., increased age, diabetes, hypertension, smoking, obesity, strong family history of CAD) prior to receiving ZOMIG. Do not administer ZOMIG if there is evidence of CAD or coronary artery vasospasm [see Contraindications (4)]. For patients with multiple cardiovascular risk factors who have a negative cardiovascular evaluation, consider administrating the first ZOMIG dose in a medically-supervised setting and performing an electrocardiogram (ECG) immediately following ZOMIG administration. For such patients, consider periodic cardiovascular evaluation in intermittent long-term users of ZOMIG.

5.2 Arrhythmias

Life-threatening disturbances of cardiac rhythm including ventricular tachycardia and ventricular fibrillation leading to death have been reported within a few hours following the administration of 5-HT1 agonists. Discontinue ZOMIG if these disturbances occur. Patients with Wolff-Parkinson-White Syndrome or arrhythmias associated with other cardiac accessory conduction pathway disorders should not receive ZOMIG [see Contraindications (4)].

5.3 Chest, Throat, Neck and/or Jaw Pain/Tightness/Pressure

As with other 5-HT1 agonists, sensations of tightness, pain, pressure, and heaviness in the precordium, throat, neck, and jaw commonly occur after treatment with ZOMIG and is usually non-cardiac in origin. However, if a cardiac origin is suspected, patients should be evaluated. Patients shown to have CAD and those with Prinzmetal's variant angina should not receive 5-HT1 agonists [see Contraindications (4)].

5.4 Cerebrovascular Events

Cerebral hemorrhage, subarachnoid hemorrhage, and stroke have occurred in patients treated with 5-HT1 agonists, and some have resulted in fatalities. In a number of cases, it appears possible that the cerebrovascular events were primary, the 5-HT1 agonist having been administered in the incorrect belief that the symptoms experienced were a consequence of migraine, when they were not. Discontinue ZOMIG if a cerebrovascular event occurs.

As with other acute migraine therapies, before treating headaches in patients not previously diagnosed as migraineurs, and in migraineurs who present with symptoms atypical for migraine, other potentially serious neurological conditions should be excluded. ZOMIG should not be administered to patients with a history of stroke or transient ischemic attack [see Contraindications (4)].

5.5 Other Vasospasm Reactions

5-HT1 agonists, including ZOMIG, may cause non-coronary vasospastic reactions, such as peripheral vascular ischemia, gastrointestinal vascular ischemia and infarction (presenting with abdominal pain and bloody diarrhea), splenic infarction, and Raynaud's syndrome. In patients who experience symptoms or signs suggestive of vasospasm reaction following the use of any 5-HT1 agonist, the suspected vasospasm reaction should be ruled out before receiving additional ZOMIG doses [see Contraindications (4)].

Reports of transient and permanent blindness and significant partial vision loss have been reported with the use of 5-HT1 agonists. Since visual disorders may be part of a migraine attack, a causal relationship between these events and the use of 5-HT1 agonists have not been clearly established.

5.6 Medication Overuse Headache

Overuse of acute migraine drugs (e.g. ergotamine, triptans, opioids, or a combination of drugs for 10 or more days per month) may lead to exacerbation of headache (medication overuse headache). Medication overuse headache may present as migraine-like daily headaches, or as a marked increase in frequency of migraine attacks. Detoxification of patients, including withdrawal of the overused drugs, and treatment of withdrawal symptoms (which often includes a transient worsening of headache) may be necessary.

5.7 Serotonin Syndrome

Serotonin syndrome may occur with triptans, including ZOMIG, particularly during co-administration with selective serotonin reuptake inhibitors (SSRIs), serotonin norepinephrine reuptake inhibitors (SNRIs), tricyclic antidepressants (TCAs), and MAO inhibitors [see Drug Interactions (7.5)]. Serotonin syndrome symptoms may include mental status changes (e.g., agitation, hallucinations, coma), autonomic instability (e.g., tachycardia, labile blood pressure, hyperthermia), neuromuscular aberrations (e.g., hyperreflexia, incoordination), and/or gastrointestinal symptoms (e.g., nausea, vomiting, diarrhea). The onset of symptoms usually rapidly occurs within minutes to hours of receiving a new or a greater dose of a serotonergic medication. ZOMIG treatment should be discontinued if serotonin syndrome is suspected [see Drug Interactions (7.5) and Patient Counseling Information (17)].

5.8 Increase in Blood Pressure

Significant elevations in systemic blood pressure have been reported in patients treated with 5-HT1 agonists including patients without a history of hypertension. Very rarely these increases in blood pressure have been associated with significant clinical events. In healthy subjects treated with 5 mg of ZOMIG oral tablet, an increase of 1 and 5 mm Hg in the systolic and diastolic blood pressure, respectively, was seen. In a study of patients with moderate to severe liver impairment, 7 of 27 patients experienced 20 to 80 mm Hg elevations in systolic and/or diastolic blood pressure after a dose of 10 mg of ZOMIG oral tablet. As with all triptans, blood pressure should be monitored in ZOMIG-treated patients. ZOMIG is contraindicated in patients with uncontrolled hypertension [see Contraindications (4)].

6 ADVERSE REACTIONS

The following adverse reactions are discussed in more detail in other sections of labeling:

- Myocardial Ischemia, Myocardial Infarction, and Prinzmetal's Angina [see Warnings and Precautions (5.1)]
- Arrhythmias [see Warnings and Precautions (5.2)]
- Chest, Throat, Neck and/or Jaw Pain/Tightness/Pressure [see Warnings and Precautions (5.3)]
- Cerebrovascular Events [see Warnings and Precautions (5.4)]
- Other Vasospasm Reactions [see Warnings and Precautions (5.5)]
- Medication Overuse Headache [see Warnings and Precautions (5.6)]
- Serotonin Syndrome [see Warnings and Precautions (5.7)]
- Increase in Blood Pressure [see Warnings and Precautions (5.8)]

6.1 Clinical Trials Experience

Because clinical studies are conducted under widely varying conditions, adverse reaction rates observed in the clinical studies of a drug cannot be directly compared to rates in the clinical studies of another drug and may not reflect the rates observed in practice.

Adults
Among 460 patients treating 1180 single attacks with ZOMIG nasal spray in a blinded placebo controlled trial (Study 1), there was a low withdrawal rate related to adverse reactions: 5 mg (1.3%), 2.5 mg (0%), and placebo (0.4%). None of the withdrawals were due to a serious event. One patient was withdrawn due to abnormal ECG changes from baseline that were incidentally found 23 days after the last dose of ZOMIG nasal spray.

The most common adverse reactions (≥ 5% and > placebo) in any dosage strength in clinical trials for ZOMIG nasal spray were: unusual taste, paresthesia, hyperesthesia, and dizziness. The incidence of adverse reactions was generally dose-related.

Table 1 lists the adverse reactions from the controlled clinical trial (Study 1) that occurred in ≥ 2% of patients in either the 2.5 or 5 mg ZOMIG nasal spray dose groups and with an incidence greater than placebo.

Table 1: Adverse reactions In a Placebo-Controlled Study In Adult Patients with Migraine (Study 1)

Body System Adverse Reaction | Placebo (N=228) | ZOMIG 2.5 mg (N=224) | ZOMIG 5 mg (N=236)
Atypical Sensations
Hyperesthesia | 0% | 1% | 5%
Paraesthesia | 6% | 5% | 10%
Warm Sensation | 2% | 4% | 0%
Ear/Nose/Throat
Disorder/Discomfort of nasal cavity | 2% | 1% | 3%
Pain and Pressure Sensations
Pain Location Specified | 1% | 2% | 4%
Throat Pain | 1% | 4% | 4%
Throat Tightness | 1% | <1% | 2%
Digestive
Dry Mouth | <1% | 3% | 2%
Nausea | 1% | 1% | 4%
Neurological
Dizziness | 4% | 6% | 3%
Somnolence | 2% | 1% | 4%
Other
Unusual Taste | 3% | 17% | 21%
Asthenia | 1% | 3% | 3%

In Study 1, adverse reactions occurring in ≥ 1% and < 2% of patients in all attacks in either ZOMIG nasal spray dose group and with incidence greater than that of placebo were: abdominal pain, chills, throat pressure, facial edema, chest pressure, palpitation, dysphagia, arthralgia, myalgia, and depersonalization.

The incidence of adverse reactions in controlled clinical trials was not affected by gender, weight, or age of the patients (18-39 vs. 40-65 years of age), or presence of aura. There were insufficient data to assess the impact of race on the incidence of adverse reactions.

Local Adverse Reactions:
Among 460 patients using ZOMIG 2.5 mg or 5 mg in the controlled clinical trial, approximately 3% noted local irritation or soreness at the site of administration. Adverse reactions of any kind, perceived in the nasopharynx (which may include systemic effects of triptans) were severe in about 1% of patients and approximately 57% resolved in 1 hour. Nasopharyngeal examinations, in a subset of patients participating in two long term trials of up to one-year duration, failed to demonstrate any clinically significant changes with repeated use of ZOMIG nasal spray.

All nasopharyngeal adverse reactions with an incidence of ≥ 2% of patients in any ZOMIG nasal spray dose groups are included in Table 1.

Other Adverse Reactions:
In the paragraphs that follow, the frequencies of less commonly reported adverse clinical reactions are presented. Because the reports include reactions observed in open and uncontrolled studies, the role of ZOMIG in their causation cannot be reliably determined. Furthermore, variability associated with adverse reaction reporting, the terminology used to describe adverse reactions, etc., limit the value of the quantitative frequency estimates provided. Reaction frequencies are calculated as the number of patients who used ZOMIG nasal spray and reported a reaction divided by the total number of patients exposed to ZOMIG nasal spray (n=3059). All reported reactions are included except those already listed in the previous table, those too general to be informative, and those not reasonably associated with the use of the drug. Reactions are further classified within body system categories and enumerated in order of decreasing frequency using the following definitions: infrequent adverse reactions are those occurring in 1/100 to 1/1,000 patients and rare adverse reactions are those occurring in fewer than 1/1,000 patients.

General: Infrequent: allergic reactions.
Cardiovascular: Infrequent: arrhythmias, hypertension, syncope and tachycardia. Rare: angina pectoris and myocardial infarct.
Digestive: Rare: stomatitis.
Neurological: Infrequent: agitation, amnesia, anxiety, depression, insomnia, and nervousness. Rare: convulsions.
Respiratory: Infrequent: bronchitis, increased cough, dyspnea, epistaxis, laryngeal edema, pharyngitis, rhinitis, and sinusitis.
Skin: Infrequent: pruritus, rash, and urticaria.
Urogenital: Infrequent: polyuria and urinary urgency. Rare: urinary frequency.
Special senses: Infrequent: tinnitus. Rare: conjunctivitis, dry eye, and visual field defect.

The adverse reaction profile seen with ZOMIG nasal spray is similar to that seen with ZOMIG tablets and ZOMIG-ZMT tablets except for the occurrence of local adverse reactions from the nasal spray (see ZOMIG tablet/ZOMIG-ZMT oral disintegrating tablet Prescribing Information).

Pediatric Patients 12 to 17 Years of Age
The safety of ZOMIG nasal spray in the acute treatment of migraine in pediatric patients 12 to 17 years of age was established in two studies [see Pediatric Use (8.4) and Clinical Studies (14.2)]. The most common adverse reactions (incidence of ≥ 2% of pediatric patients receiving 2.5 mg and 5 mg ZOMIG nasal spray and numerically greater than placebo) after a single dose are summarized in Table 2. Dysgeusia (unusual taste) was the most common adverse reaction, with a numerically greater incidence for patients receiving ZOMIG compared to placebo (10% vs. 2%). Other common adverse reactions were nasal discomfort, dizziness, oropharyngeal pain, and nausea.

Table 2 lists the adverse reactions from the pooled placebo-controlled studies that occurred in ≥ 2% of pediatric patients 12 to 17 years of age in either the 2.5 mg or 5 mg ZOMIG dose groups and with an incidence greater than placebo.

Table 2: Adverse reactions in Pooled Placebo-Controlled Studies In Pediatric Patients 12 to 17years of Age with Migraine

Adverse Reaction | Placebo (N=437) | ZOMIG 2.5 mg (N=81) | ZOMIG 5 mg (N=431)
Unusual taste | 2% | 6% | 10%
Nasal discomfort | 1% | 3% | 3%
Dizziness | 1% | 0% | 2%
Oropharyngeal pain | 2% | 0% | 2%
Nausea | 1% | 1% | 2%

The adverse reaction profile was similar across gender. There were insufficient data to assess the impact of race on the incidence of adverse reactions.

6.2 Postmarketing Experience

The following adverse reactions were identified during post approval use of ZOMIG. Because these reactions are reported voluntarily from a population of uncertain size, it is not always possible to reliably estimate their frequency or establish a causal relationship to drug exposure.

The reactions enumerated include all except those already listed in the Clinical Trials Experience section above or the Warnings and Precautions section.

Hypersensitivity Reactions:
There have been reports of anaphylaxis, anaphylactoid, and hypersensitivity reactions including angioedema in patients receiving ZOMIG. ZOMIG is contraindicated in patients with a history of hypersensitivity reaction to ZOMIG.

7 DRUG INTERACTIONS

7.1 Ergot-containing drugs

Ergot-containing drugs have been reported to cause prolonged vasospastic reactions. Because these effects may be additive, use of ergotamine-containing or ergot-type medications (like dihydroergotamine or methysergide) and ZOMIG within 24 hours of each other is contraindicated [see Contraindications (4)].

7.2 MAO-A Inhibitors

MAO-A inhibitors increase the systemic exposure of zolmitriptan. Therefore, the use of ZOMIG in patients receiving MAO-A inhibitors is contraindicated [see Contraindications (4) and Clinical Pharmacology (12.3)].

7.3 5-HT1B/1D agonists (e.g. triptans)

Concomitant use of other 5-HT1B/1D agonists (including triptans) within 24 hours of ZOMIG treatment is contraindicated because the risk of vasospastic reactions may be additive [see Contraindications (4)].

7.4 Cimetidine

Following administration of cimetidine, the half-life and AUC of ZOMIG and its active metabolites were approximately doubled [see Clinical Pharmacology (12.3)]. If cimetidine and ZOMIG are used concomitantly, limit the maximum single dose of ZOMIG to 2.5 mg, not to exceed 5 mg in any 24-hour period [see Dosage and Administration (2.3) and Clinical Pharmacology (12.3)].

7.5 Selective Serotonin Reuptake Inhibitors/Serotonin Norepinephrine Reuptake Inhibitors and Serotonin Syndrome

Cases of life-threatening serotonin syndrome have been reported during combined use of selective serotonin reuptake inhibitors (SSRIs) or serotonin norepinephrine reuptake inhibitors (SNRIs) and triptans [see Warnings and Precautions (5.7)].

8 USE IN SPECIFIC POPULATIONS

8.1 Pregnancy

Risk Summary
There are no adequate data on the developmental risk associated with the use of ZOMIG in pregnant women. In reproductive toxicity studies in rats and rabbits, oral administration of zolmitriptan to pregnant animals resulted in embryolethality and fetal abnormalities (malformations and variations) at clinically relevant exposures.

In the U.S. general population, the estimated background risk of major birth defects and miscarriage in clinically recognized pregnancies is 2% to 4% and 15% to 20%, respectively. The estimated rates of major birth defects (2.2%-2.9%) and miscarriage (17%) among deliveries to women with migraine are similar to rates reported in women without migraine.

Clinical Considerations
Disease-Associated Maternal and/or Embryo/Fetal Risk

Published data have suggested that women with migraine may be at increased risk of preeclampsia during pregnancy.

Data
Animal Data
When zolmitriptan was administered to pregnant rats during the period of organogenesis at oral doses of 100, 400, and 1200 mg/kg/day (plasma exposures (AUCs) ≈280, 1100, and 5000 times the human AUC at the maximum recommended human dose (MRHD) of 10 mg/day), there was a dose-related increase in embryolethality. A no-effect dose for embryolethality was not established. When zolmitriptan was administered to pregnant rabbits during the period of organogenesis at oral doses of 3, 10, and 30 mg/kg/day (plasma AUCs ≈1, 11, and 42 times the human AUC at the MRHD), there were increases in embryolethality and in fetal malformations and variations. The no-effect dose for adverse effects on embryo-fetal development was associated with a plasma AUC similar to that in humans at the MRHD. When female rats were given zolmitriptan during gestation, parturition, and lactation at oral doses of 25, 100, and 400 mg/kg/day (plasma AUCs ≈70, 280, and 1100 times that in human at the MRHD), an increased incidence of hydronephrosis was found in the offspring. The no-effect dose was associated with a plasma AUC ≈280 times that in humans at the MRHD.

8.2 Lactation

Risk Summary
There are no data on the presence of zolmitriptan or its metabolites in human milk, the effects on the breastfed infant, or the effects of zolmitriptan and its metabolites on milk production. In rats, oral dosing with zolmitriptan resulted in levels in milk up to 4 times that in maternal plasma.

The developmental and health benefits of breastfeeding should be considered along with the mother's clinical need for ZOMIG and any potential adverse effects on the breastfed infant from ZOMIG or from the underlying maternal condition.

8.4 Pediatric Use

Safety and effectiveness of ZOMIG in pediatric patients under 12 years of age have not been established.

The efficacy of ZOMIG nasal spray in the acute treatment of migraine in pediatric patients 12 to 17 years of age was established in a placebo-controlled study with a total of 81 pediatric patients receiving ZOMIG 2.5 mg and 229 pediatric patients receiving ZOMIG 5 mg [see Clinical Studies (14.2)].

In an earlier study with a different design, ZOMIG 5 mg nasal spray was evaluated in the acute treatment of migraine headache in 171 pediatric patients 12 to 17 years of age. In that study, the efficacy of ZOMIG nasal spray was not established.

The safety of ZOMIG nasal spray in the acute treatment of migraine in pediatric patients 12 to 17 years of age was established in two placebo-controlled studies with a total of 81 pediatric patients receiving ZOMIG 2.5 mg and 431 pediatric patients receiving ZOMIG 5 mg [see Adverse Reactions (6.1)].

The safety profile of ZOMIG nasal spray in pediatric patients 12 to 17 years of age is similar to the profile observed in adults [see Adverse Reactions (6.1)].

In the postmarketing experience with triptans, including ZOMIG, there is a limited number of reports that describe pediatric patients who have experienced clinically serious adverse events; those that were reported are similar in nature to those reported rarely in adults.

8.5 Geriatric Use

Clinical studies of ZOMIG did not include sufficient numbers of subjects aged 65 and over to determine whether they respond differently from younger subjects. Other reported clinical experience has not identified differences in responses between the elderly and younger patients. In general, dose selection for an elderly patient should be cautious, usually starting at the low end of the dosing range, reflecting the greater frequency of decreased hepatic, renal, or cardiac function, and of concomitant disease or other drug therapy. Geriatric patients who have other cardiovascular risk factors (e.g., diabetes, hypertension, smoking, obesity, strong family history of coronary artery disease) should have a cardiovascular evaluation prior to receiving ZOMIG [see Warnings and Precautions (5.1)]. The pharmacokinetics of zolmitriptan were similar in geriatric patients (aged > 65 years) compared to younger patients [see Clinical Pharmacology (12.3)].

8.6 Hepatic Impairment

The effect of hepatic disease on the pharmacokinetics of zolmitriptan nasal spray has not been evaluated. After oral administration, zolmitriptan blood levels were increased in patients with moderate to severe hepatic impairment, and significant elevation in blood pressure was observed in some of these patients [see Warnings and Precautions (5.8)]. ZOMIG nasal spray is not recommended in patients with moderate to severe hepatic impairment [see Dosage and Administration (2.2) and Clinical Pharmacology (12.3)].

10 OVERDOSAGE

There is no experience with acute overdose. Clinical study subjects receiving single 50 mg oral doses of zolmitriptan commonly experienced sedation.

The elimination half-life of ZOMIG is 3 hours [see Clinical Pharmacology (12.1)] and therefore monitoring of patients after overdose with ZOMIG should continue for at least 15 hours or while symptoms or signs persist.

There is no specific antidote to zolmitriptan. In cases of severe intoxication, intensive care procedures are recommended, including establishing and maintaining a patent airway, ensuring adequate oxygenation and ventilation, and monitoring and support of the cardiovascular system.

It is unknown what effect hemodialysis or peritoneal dialysis has on the plasma concentrations of zolmitriptan.

11 DESCRIPTION

ZOMIG® (zolmitriptan) Nasal Spray contains zolmitriptan, which is a selective 5-hydroxytryptamine 1B/1D (5-HT1B/1D) receptor agonist. Zolmitriptan is chemically designated as (S)-4-[[3-[2-(dimethylamino) ethyl]-1H-indol-5-yl]methyl]-2-oxazolidinone and has the following chemical structure:

The empirical formula is C16H21N3O2, representing a molecular weight of 287.36. Zolmitriptan is a white to almost white powder that is readily soluble in water. ZOMIG Nasal Spray is supplied as a clear to pale yellow solution of zolmitriptan, buffered to a pH 5.0. Each ZOMIG Nasal Spray contains 2.5 mg or 5 mg of zolmitriptan in a 100-μL unit dose aqueous buffered solution containing citric acid, anhydrous, USP, disodium phosphate dodecahydrate USP and purified water USP.

ZOMIG Nasal Spray is hypertonic. The osmolarity of ZOMIG Nasal Spray for 2.5 mg is 360 to 420 mOsmol, and for 5 mg is 420 to 470 mOsmol.

12 CLINICAL PHARMACOLOGY

12.1 Mechanism of Action

Zolmitriptan binds with high affinity to human recombinant 5-HT1D and 5-HT1B receptors, and moderate affinity for 5-HT1A receptors. The N-desmethyl metabolite also has high affinity for 5-HT1B/1D and moderate affinity for 5-HT1A receptors.

Current theories proposed to explain the etiology of migraine headache suggest that symptoms are due to local cranial vasodilatation and/or to the release of sensory neuropeptides (vasoactive intestinal peptide, substance P and calcitonin gene-related peptide) through nerve endings in the trigeminal system. The therapeutic activity of ZOMIG for the treatment of migraine headache is thought to be due to the agonist effects at the 5-HT1B/1D receptors on intracranial blood vessels (including the arterio-venous anastomoses) and sensory nerves of the trigeminal system which result in cranial vessel constriction and inhibition of pro-inflammatory neuropeptide release.

12.3 Pharmacokinetics

Absorption, Distribution, Metabolism, and Excretion Absorption
Zolmitriptan nasal spray is rapidly absorbed via the nasopharynx as detected in a Photon Emission Tomography (PET) study using ^11C zolmitriptan. The mean relative bioavailability of the nasal spray formulation is 102%, compared with the oral tablet. Zolmitriptan was detected in plasma by 5 minutes and peak plasma concentration generally was achieved by 3 hours. The time at which maximum plasma concentrations were observed was similar after single (1 day) or multiple (4 days) nasal dosing. Plasma concentrations of zolmitriptan are sustained for 4 to 6 hours after dosing. Zolmitriptan and its active N-desmethyl metabolite display linear kinetics after single or multiple doses of ZOMIG nasal spray over the dose range of 0.1 to 10 mg.

The pharmacokinetics of the N-desmethyl metabolite are similar to that of zolmitriptan for all nasal spray dosages. The N-desmethyl metabolite is detected in plasma by 15 minutes and peak plasma concentration is generally achieved by 3 hours after administration.

Food has no significant effect on the bioavailability of zolmitriptan.

Distribution
Plasma protein binding of zolmitriptan is 25% over the concentration range of 10-1000 ng/mL. The mean apparent volume of distribution for zolmitriptan nasal spray formulation is 8.4 L/kg.

Metabolism
Zolmitriptan is converted to an active N-desmethyl metabolite such that the metabolite concentrations are about two-thirds that of zolmitriptan. Because the 5HT1B/1D potency of the metabolite is 2 to 6 times that of the parent compound, the metabolite may contribute a substantial portion of the overall effect after ZOMIG administration.

Excretion
The mean elimination half-life for zolmitriptan and N-desmethyl metabolite following single or multiple nasal spray administration are approximately 3 hours, similar to the half-life values seen after oral tablet administration.

In a study with orally administered zolmitriptan, total radioactivity recovered in urine and feces was 65% and 30% of the administered dose, respectively. In urine, unchanged zolmitriptan and N-desmethyl metabolite accounted for 8% and 4% of the dose, respectively, whereas the inactive indole acetic acid and N-oxide metabolites accounted for 31% and 7% of the dose, respectively.

Mean total plasma clearance for zolmitriptan nasal spray is 25.9 mL/min/kg, of which one-sixth is renal clearance. The renal clearance is greater than the glomerular filtration rate suggesting renal tubular secretion.

Specific Populations

Age:
The pharmacokinetics of orally administered zolmitriptan in healthy elderly non-migraineur volunteers (age 65-76 yrs) was similar to those in younger non-migraineur volunteers (age 18-39 yrs).

Sex:
Mean plasma concentrations of orally administered zolmitriptan were up to 1.5-fold higher in females than males.

Race:
There are no significant differences in the pharmacokinetics of orally administered zolmitriptan in Japanese and Caucasians.

Renal Impairment:
The effect of renal impairment on the pharmacokinetics of zolmitriptan nasal spray has not been evaluated. After orally dosing zolmitriptan, renal clearance was reduced by 25% in patients with severe renal impairment (Clcr ≥ 5 ≤ 25 mL/min) compared with the normal group (Clcr ≥ 70 mL/min); no significant change in clearance was observed in the moderately renally impaired group (Clcr ≥ 26 ≤ 50 mL/min).

Hepatic Impairment:
The effect of hepatic disease on the pharmacokinetics of zolmitriptan nasal spray has not been evaluated. In patients with severe hepatic impairment, the mean Cmax, Tmax, and AUC of zolmitriptan dosed orally were increased 1.5-fold, 2-fold (2 vs. 4 hours), and 3-fold, respectively, compared to subjects with normal hepatic function. Seven out of 27 patients experienced 20 to 80 mm Hg elevations in systolic and/or diastolic blood pressure after a 10 mg ZOMIG dose [see Dosage and Administration (2.2) and Use in Specific Populations (8.6)].

Hypertensive Patients:
No differences in the pharmacokinetics of oral zolmitriptan or its effects on blood pressure were seen in mild to moderate hypertensive volunteers compared with normotensive controls.

Drug Interactions
All drug interaction studies were performed in healthy volunteers using a single 10 mg dose of zolmitriptan and a single dose of the other drug except where otherwise noted. Eight drug interaction studies have been performed with zolmitriptan tablets and one study (xylometazoline) was performed with nasal spray.

Xylometazoline:
An in vivo drug interaction study with ZOMIG nasal spray indicated that 1 spray (100 μL dose) of xylometazoline (0.1% w/v), a decongestant, administered 30 minutes prior to a 5 mg nasal dose of zolmitriptan did not alter the pharmacokinetics of zolmitriptan.

Fluoxetine:
The pharmacokinetics of zolmitriptan, as well as its effect on blood pressure, were unaffected by 4 weeks of pre-treatment with oral fluoxetine (20 mg/day).

MAO Inhibitors:
Following one week of administration of moclobemide (150 mg twice-daily), a specific MAO-A inhibitor, there was an increase of about 25% in both Cmax and AUC for zolmitriptan and a 3-fold increase in the Cmax and AUC of the active N-desmethyl metabolite of zolmitriptan [see Contraindications (4) and Drug Interactions (7.2)].

Selegiline, a selective MAO-B inhibitor, at a dose of 10 mg/day for 1 week, had no effect on the pharmacokinetics of zolmitriptan and its metabolite.

Propranolol:
Cmax and AUC of zolmitriptan increased 1.5-fold after one week of dosing with propranolol (160 mg/day). Cmax and AUC of the N-desmethyl metabolite were reduced by 30% and 15%, respectively. There were no interactive effects on blood pressure or pulse rate following administration of propranolol with zolmitriptan.

Acetaminophen:
A single 1g dose of acetaminophen does not alter the pharmacokinetics of zolmitriptan and its N-desmethyl metabolite. However, zolmitriptan delayed the Tmax of acetaminophen by one hour.

Metoclopramide:
A single 10 mg dose of metoclopramide had no effect on the pharmacokinetics of zolmitriptan or its metabolites.

Oral Contraceptives:
Retrospective analysis of pharmacokinetic data across studies indicated that mean Cmax and AUC of zolmitriptan were 30% and 50% higher, respectively, and Tmax was delayed by one-half hour in females taking oral contraceptives compared to females not taking oral contraceptives. The effect of zolmitriptan on the pharmacokinetics of oral contraceptives has not been studied.

Cimetidine:
Following the administration of cimetidine, the half-life and AUC of a 5 mg dose of zolmitriptan and its active metabolite were approximately doubled. A dosage adjustment is therefore required [see Drug Interactions (7.4)].

13 NONCLINICAL TOXICOLOGY

13.1 Carcinogenesis, Mutagenesis, Impairment of Fertility

Carcinogenesis
Zolmitriptan was administered to mice and rats at doses up to 400 mg/kg/day. Mice were dosed for 85 weeks (males) and 92 weeks (females); rats were dosed for 101 weeks (males) and 86 weeks (females). There was no evidence of drug-induced tumors in mice at plasma exposures (AUC) up to approximately 700 times that in humans at the maximum recommended human dose (MRHD) of 10 mg/day. In rats, there was an increase in the incidence of thyroid follicular cell hyperplasia and thyroid follicular cell adenomas in male rats receiving 400 mg/kg/day. No increase in tumors was observed in rats at 100 mg/kg/day, a dose associated with a plasma AUC ≈700 times that in humans at the MRHD.

Mutagenesis
Zolmitriptan was positive in an in vitro bacterial reverse mutation (Ames) assay and in an in vitro chromosomal aberration assay in human lymphocytes. Zolmitriptan was negative in an in vitro mammalian gene cell mutation (CHO/HGPRT) assay and in oral in vivo micronucleus assays in mouse and rat.

Impairment of Fertility
Studies of male and female rats administered zolmitriptan prior to and during mating and up to implantation showed no impairment of fertility at oral doses up to 400 mg/kg/day. The plasma exposure (AUC) at this dose was approximately 3000 times that in humans at the MRHD.

14 CLINICAL STUDIES

14.1 Adults

The efficacy of ZOMIG nasal spray 2.5 mg and 5 mg in the acute treatment of migraine headache with or without aura in adults was demonstrated in Study 1, a randomized, outpatient, double-blind, placebo-controlled trial.

In Study 1, patients were instructed to treat a moderate to severe headache. Headache response, defined as a reduction in headache severity from moderate or severe pain to mild or no pain, was assessed 15, 30, 45 minutes and 1, 2, and 4 hours after dosing. Pain-free response rates and associated symptoms such as nausea, photophobia, and phonophobia were also assessed. A dose of escape medication was allowed 4 to 24 hours after the initial treatment for persistent and recurrent headache.

In Study 1, of the patients taking ZOMIG nasal spray 2.5 mg or 5 mg, 83% were female and 99% were Caucasian, with a mean age of 41 years (range 18 to 65 years).

The two-hour headache response rates in patients treated with ZOMIG nasal spray were significantly higher among patients receiving ZOMIG nasal spray at all doses, compared with placebo (see Table 3).

Table 3: First Attack Data: Percentage of Adult Patients with Headache Response to ZOMIG Nasal Spray (Mild or No Headache) 2 Hours Following Treatment in Study 1

PLACEBO (N=218) | ZOMIG 2.5 mg (N=219) | ZOMIG 5 mg (N=228)
31% | 55%* | 69%*

*p < 0.001 in comparison with placebo

The estimated probability of achieving an initial headache response following treatment with ZOMIG nasal spray is depicted in Figure 1.

Figure 1: Estimated probability of achieving an initial headache response after treatment in Study 1

Note: Figure 1 shows the Kaplan-Meier plot of the probability over time of obtaining headache response (moderate or severe headache improving to mild or no pain) following treatment with ZOMIG nasal spray. The estimates displayed are based on a placebo controlled, outpatient trial providing evidence of efficacy. Patients not achieving headache response or taking additional treatment prior to 4 hours were censored to 4 hours.

For patients with migraine associated photophobia, phonophobia, and nausea at baseline, there was a decreased incidence of these symptoms following administration of ZOMIG nasal spray as compared with placebo.

Four to 24 hours following the initial dose of study treatment, patients were allowed to use additional treatment for pain relief in the form of a second dose of study treatment or other medication. The estimated probability of patients taking a second dose or other medication for migraine over the 24 hours following the initial dose of study treatment is summarized in Figure 2.

Figure 2: Estimated probability of patients taking an escape medication within the 24 hours following the initial dose of study treatment in Study 1

*This Kaplan-Meier plot is based on data obtained from the placebo controlled clinical trial. Patients not using additional treatments were censored at 24 hours. The plot includes both patients who had headache response at 2 hours and those who had no response to the initial dose. It should be noted that the protocol did not allow remedication within 4 hours post dose.

The efficacy of ZOMIG was unaffected by presence of aura; presence of headache upon awakening, relationship to menses; gender, age or weight of the patient; or presence of pre-treatment nausea.

The efficacy of ZOMIG nasal spray 5 mg was further supported by an interim analysis of another similarly designed trial. The 2-hour headache response rates for the first 210 subjects in that study for ZOMIG 5 mg and placebo were 70% and 47%, respectively (N=108 and 102, respectively, p=0.0006).

14.2 Pediatric Patients 12 to 17 Years of Age

The efficacy of ZOMIG nasal spray in the acute treatment of migraine headache with or without aura in pediatrics patients 12 to 17 years of age was demonstrated in Study 2, a randomized, double-blind, placebo-controlled trial with a single-blind run-in period.

Patients had to have an established diagnosis of migraine (history indicating the presence of migraine for at least 1 year) with or without aura with a typical untreated migraine headache attack lasting 3 hours or more. The study included treatment of a single migraine headache attack with 1 dose of single-blind placebo during the 30-day run-in period. If the patient met all conditions for randomization, including a lack of response to the placebo run-in, a subsequent single migraine headache attack was treated with 1 blinded dose of either ZOMIG nasal spray 5 mg, 2.5 mg, or matching placebo.

In Study 2, of the patients taking ZOMIG nasal spray 2.5 mg or 5 mg, 62% were female and 93% were Caucasian, with a mean age of 14 years (range 12 to 17 years).

Study 2 evaluated the proportion of pediatric patients 12 to 17 years of age who had no headache pain at 2 hours following treatment. Headache response (defined as a reduction in migraine-related headache pain severity from moderate or severe pain to mild or no pain) and the absence of nausea, photophobia, and phonophobia at 2 hours post treatment were also assessed. As shown in Table 4, the percentage of pediatric patients 12 to 17 years of age with no headache pain at 2 hours following treatment was significantly higher for ZOMIG nasal spray 5 mg than placebo.

Table 4: Percentage of Pediatric Patients 12 to 17 Years of Age with No Headache Pain, With Headache Response, No Nausea, No Photophobia, and No Phonophobia Two Hours after Treatment in Study 2

Two Hours Following Treatment
 | Placebo (N=253) | ZOMIG 2.5 mg (N=81) | ZOMIG 5 mg (N=229)
No Headache Pain | 17% | 25% | 30%*
With Headache Response | 39% | 53%* | 51%*
No Photophobia | 44% | 66%* | 56%*
No Phonophobia | 48% | 61%* | 58%*
No Nausea | 66% | 70% | 72%

*p < 0.05 in comparison with placebo

Two to 24 hours following the initial dose of study treatment, patients were allowed to use their usual medication for pain relief. The estimated probability of patients taking escape medication during the first 24 hours following the initial dose of study treatment is summarized in Figure 3.

Figure 3: Estimated Probability of Pediatric Patients 12 to 17 Years of Age Taking an Escape Medication Within the 24 Hours Following the Initial Dose of Study Treatment in Study 2

16 HOW SUPPLIED/STORAGE AND HANDLING

The ZOMIG Nasal Spray device is a blue-colored plastic device with a gray protection cap, labeled to indicate the nominal dose. Each ZOMIG Nasal Spray device administers a single dose of ZOMIG.

ZOMIG Nasal Spray is supplied as a clear to pale yellow solution of zolmitriptan, buffered to a pH 5.0. Each ZOMIG Nasal Spray device contains 2.5 mg or 5 mg of zolmitriptan in a 100 μL unit dose aqueous buffered solution containing citric acid, anhydrous, USP, disodium phosphate dodecahydrate USP and purified water USP.

2.5 mg ZOMIG® Nasal Spray is supplied in boxes of 6 single-use nasal spray units. (NDC 64896-083-12).

5 mg ZOMIG® Nasal Spray is supplied in boxes of 6 single-use nasal spray units. (NDC 64896-084-12).

Each ZOMIG® Nasal Spray single dose unit spray supplies 2.5 and 5 mg, respectively, of zolmitriptan. The ZOMIG® Nasal Spray unit must be discarded after use.

Store at controlled room temperature, 20-25°C (68-77°F) [see USP].

17 PATIENT COUNSELING INFORMATION

Advise the patient to read the FDA-approved patient labeling (Patient lnformation).

Risk of Myocardial Ischemia and/or Infarction, Prinzmetal's angina, Other Vasospasm-related Events, and Cerebrovascular Events

Inform patients that ZOMIG may cause serious cardiovascular side effects such as myocardial infarction or stroke, which may result in hospitalization and even death. Although serious cardiovascular events can occur without warning symptoms, patients should be alert for the signs and symptoms of chest pain, shortness of breath, weakness, slurring of speech, and should ask for medical advice when observing any indicative sign or symptoms [see Warnings and Precautions (5.1, 5.2, 5.4, 5.5)].

Medication Overuse Headache
Inform patients that use of acute migraine drugs for 10 or more days per month may lead to an exacerbation of headache, and encourage patients to record headache frequency and drug use (e.g., by keeping a headache diary) [see Warnings and Precautions (5.6)].

Serotonin Syndrome
Inform patients about the risk of serotonin syndrome with the use of ZOMIG or other triptans, particularly during combined use with selective serotonin reuptake inhibitors (SSRIs) or serotonin norepinephrine reuptake inhibitors (SNRIs) [see Warnings and Precautions (5.7)].

Pregnancy
Advise patients to notify their healthcare provider if they are pregnant or plan to become pregnant.

Lactation
Advise patients to notify their healthcare provider if they are breastfeeding or plan to breastfeed [see Use in Specific Populations (8.2)].

Handling of ZOMIG nasal spray device
The ZOMIG Nasal Spray device is packaged in a carton and is a blue-colored plastic device with a gray protection cap, labeled to indicate the nominal dose. Caution patients to not remove the gray protection cap until prior to dosing. The ZOMIG Nasal Spray device is placed in a nostril and actuated to deliver a single dose. Caution patients to avoid spraying the contents of the device in their eyes.

Patient Information

ZOMIG® (Zo-mig)
(zolmitriptan)
Nasal Spray

Please read this information before you start taking ZOMIG Nasal Spray and each time you renew your prescription just in case anything has changed. Remember, this summary does not take the place of discussions with your doctor. You and your doctor should discuss ZOMIG Nasal Spray when you start taking your medication and at regular checkups.

What is ZOMIG Nasal Spray?
ZOMIG Nasal Spray is a prescription medicine used to treat migraine headaches with or without aura in adults and pediatric patients (12 to 17 years of age).

ZOMIG Nasal Spray is not for other types of headaches.

ZOMIG Nasal Spray is not for the prevention of migraine headaches.

It is not known if ZOMIG Nasal Spray is safe and effective to treat cluster headaches.

ZOMIG Nasal Spray is not for people with moderate or severe liver problems (hepatic impairment).

It is not known if ZOMIG Nasal Spray is safe and effective in children under 12 years of age.

Who should not use ZOMIG Nasal Spray?

Do not use ZOMIG Nasal Spray if you have:

- heart problems, a history of heart problems, or problems with the electrical system of your heart had a stroke, transient ischemic attacks (TIAs), or problems with your blood circulation
- hemiplegic migraines or basilar migraines. If you are not sure if you have these types of migraines, ask your healthcare provider.
- narrowing of blood vessels to your legs, arms, or stomach (peripheral vascular disease)
- uncontrolled high blood pressure
- used certain medicines called 5-HT1 agonists ('triptans") such as almotriptan (AXERT®), eletriptan (RELPAX®), frovatriptan (FROVA®), naratriptan (AMERGE®), rizatriptan (MAXALT®), sumatriptan (IMITREX®), sumatriptan/naproxen (TREXIMET®); medicines that contain ergotamine, or ergot medicines such as BELLERGAL-S®, CAFERGOT®,
  ERGOMAR®, WIGRAINE®; dihydroergotamine like D.H.E. 45® or MIGRANAL®; or methysergide (SANSERT®) in the last 24 hours. Ask your doctor or pharmacist for a list of these medicines if you are not sure.
- are taking a monoamine oxidase A inhibitor (MAO-A inhibitor) or you stopped taking a MAO-A inhibitor in the last 14 days. Ask your doctor if you are not sure if you take an MAO-A inhibitor such as phenelzine sulfate (NARDIL®) or tranylcypromine sulfate (PARNATE®).
- are allergic to zolmitriptan or any of the ingredients in ZOMIG Nasal Spray.
  See the end of this leaflet for a complete list of ingredients in ZOMIG Nasal Spray.

What should I tell my doctor before using ZOMIG Nasal Spray?

Before using ZOMIG Nasal Spray, tell your doctor about all of your medical conditions, including if you:

- have high blood pressure
- have high cholesterol
- have diabetes
- smoke
- are overweight
- are a female who has gone through menopause
- have heart disease or a family history of heart disease or stroke
- have liver problems
- are pregnant or plan to become pregnant. It is not known if ZOMIG Nasal Spray will harm your unborn baby.
- are breastfeeding or plan to breastfeed. It is not known if ZOMIG Nasal Spray passes into your breast milk. Talk to your doctor about the best way to feed your baby while using ZOMIG Nasal Spray.

Tell your doctor about all the medicines you take, including prescription and over-the-counter medicines, vitamins, and herbal supplements.

Especially tell your doctor if you take:

- medicines used to treat mood disorders, including selective serotonin reuptake inhibitors (SSRIs), serotonin norepinephrine reuptake inhibitors (SNRIs) or monoamine oxidase inhibitors (MAOIs).
- cimetidine

How should I use ZOMIG NASAL Spray?

For detailed instructions, see the step-by-step instructions for using ZOMIG Nasal Spray at the end of this Patient Information.

- Certain people should take their first dose of ZOMIG Nasal Spray in their doctor's office or in another medical setting. Ask your doctor if you should take your first dose in a medical setting.
- Use ZOMIG Nasal Spray exactly as your doctor tells you to use it.
- Your doctor may change your dose. Do not change your dose without first talking with your doctor. If your headache comes back after using one nasal spray or you only get some relief from your headache, you can use another nasal spray 2 hours after the previous nasal spray.
- Do not use more than a total of 10 mg of ZOMIG Nasal Spray in any 24-hour period.
- It is not known if it is safe and effective to use ZOMIG Nasal Spray for more than 4 headaches in 30 days.
- Some people who use too much ZOMIG Nasal Spray may have worse headaches (medication overuse headaches). If your headaches get worse, your doctor may decide to stop your treatment with ZOMIG Nasal Spray.
- If you use too much ZOMIG Nasal Spray, call your doctor or go to the nearest hospital emergency room right away.
- You should write down when you have headaches and when you take ZOMIG Nasal Spray so you can talk to your doctor about how ZOMIG Nasal Spray is working for you.

What should I avoid while using ZOMIG Nasal Spray?

ZOMIG Nasal Spray can cause dizziness, weakness, or drowsiness. If you have these symptoms do not drive a car, use machinery, or do anything that needs you to be alert.

What are the possible side effects of ZOMIG Nasal Spray?

ZOMIG Nasal Spray can cause serious side effects. Call your doctor right away if you have any of the following symptoms after using ZOMIG Nasal Spray:

- Heart attack and other heart problems. Heart problems may lead to death. Stop taking ZOMIG Nasal Spray and get emergency medical help right away if you have any of the following symptoms of a heart attack or other heart problems:

- discomfort in the center of your chest that lasts for more than a few minutes, or that goes away and comes back
- chest pain or chest discomfort that feels like heavy pressure, squeezing, or fullness
- pain or discomfort in your arms, back, neck, jaw, or stomach
- shortness of breath with or without chest discomfort
- breaking out in a cold sweat
- feeling lightheaded
- nausea or vomiting with any of the symptoms included above

- stroke. Symptoms of stroke include face drooping, slurred speech, and unusual weakness or numbness.
- changes in color or sensation in your fingers and toes (Raynaud's syndrome)
- stomach and intestinal problems (gastrointestinal and colonic ischemic events). Symptoms of gastrointestinal and colonic ischemic events include:

- sudden or severe stomach pain
- stomach pain after meals
- weight loss
- nausea or vomiting
- constipation or diarrhea
- bloody diarrhea
- fever

- problems with blood circulation to your legs and feet (peripheral vascular ischemia). Symptoms of peripheral vascular ischemia include:

- cramping and pain in your legs or hips
- feeling of heaviness or tightness in your leg muscles
- burning or aching pain in your feet or toes while resting
- numbness, tingling, or weakness in your legs
- cold feeling or color changes in 1 or both legs or feet

- serotonin syndrome. Serotonin syndrome is a serious and life-threatening problem that can happen in people using ZOMIG Nasal Spray, especially if ZOMIG Nasal Spray is used with anti-depressant medicines called selective serotonin reuptake inhibitors (SSRIs) or selective norephinephrine reuptake inhibitors (SNRIs).

Ask your doctor or pharmacist for a list of these medicines if you are not sure.

Call your doctor right away if you have any of the following symptoms of serotonin syndrome:

- mental changes such as seeing things that are not there (hallucinations), agitation, or coma
- fast heartbeat
- changes in blood pressure
- high body temperature
- tight muscles
- trouble walking
- nausea, vomiting, or diarrhea

- increased blood pressure
- allergic reactions. Symptoms of an allergic reaction include:

- rash
- hives
- itching
- swelling of the face, mouth throat, or tongue
- difficulty breathing

The most common side effects of ZOMIG Nasal Spray are:

- unusual taste
- numbness
- dizziness
- skin sensitivity (hyperparesthesia)

These are not all the possible side effects of ZOMIG Nasal Spray. For more information ask your doctor or pharmacist.

Call your doctor for medical advice about side effects. You may report side effects to FDA at 1-800-FDA-1088.

How should I store ZOMIG Nasal Spray?

Store ZOMIG Nasal Spray at room temperature between 68°F to 77°F (20°C -25°C).

Keep ZOMIG Nasal Spray and all medicines out of the reach of children.

General information about the safe and effective use of ZOMIG Nasal Spray.

Medicines are sometimes prescribed for purposes other than those listed in Patient Information leaflets. Do not use ZOMIG Nasal Spray for a condition for which it was not prescribed. Do not give ZOMIG Nasal Spray to other people, even if they have the same symptoms that you have. It may harm them.

This leaflet summarizes the most important information about ZOMIG Nasal Spray. If you would like more information, talk to your doctor. You can ask your pharmacist or doctor for information about ZOMIG Nasal Spray that is written for health professionals.

For more information go to www.ZOMIG.com or call 1-877-835-5472.

What are the Ingredients in ZOMIG Nasal Spray?

Active ingredient: zolmitriptan

Inactive ingredients: anhydrous citric acid, dibasic sodium phosphate, and purified water

Instructions for Use

ZOMIG® (Zo-mig)
(zolmitriptan)
Nasal Spray

Important: For use in your nose only. Do not spray in your eyes.

Note: There is only 1 dose in the nasal sprayer. Do not try to prime the nasal sprayer or you will lose the dose. Do not press the plunger until you have put the tip into your nostril or you will lose the dose.

Steps for using ZOMIG Nasal Spray

Step 1. Remove the ZOMIG Nasal Spray unit from the single use package it comes in. Do not remove the unit until you are ready to use it. The unit contains only 1 spray.

Step 2. Blow your nose gently to clear your nasal passages before use.

Step 3. Remove the protective cap (See Figure A).

Step 4. Keeping your head in an upright position, gently close 1 nostril with your index finger and breathe out gently through your mouth. (See Figure B). Either nostril can be used.

Step 5. With your other hand, hold the container with your thumb supporting the container at the bottom, and your index and middle fingers on each side of the nozzle. (See Figure C).

Insert the tip of the sprayer device into your open nostril as far as feels comfortable and tilt your head slightly (See Figure D).

Do not press the plunger yet.

Step 6. Breathe in gently through your nose and at the same time press the plunger firmly with your thumb to release your dose of ZOMIG Nasal Spray (See Figure D).

The plunger may feel stiff and you may hear a click. Keep your head slightly tilted back and remove the tip from your nose. Breathe gently through your mouth for 5 to 10 seconds. You may feel liquid in your nose or the back of your throat. This is normal.

Step 7. Dispose the ZOMIG Nasal Spray device after completing the full dose or as soon as it becomes outdated or no longer needed. Dispose of properly. Keep out of reach of children. Do not reuse.

This Patient Information and Instructions for Use have been approved by the U.S. Food and Drug Administration.

ZOMIG is a registered trademark of the AstraZeneca group of companies.

Other brands mentioned are trademarks of their respective owners and are not trademarks of the AstraZeneca group of companies. The makers of these brands are not affiliated with AstraZeneca or its products.

Revised 04/2019

Distributed by:
Amneal Specialty, a division of Amneal Pharmaceuticals LLC
Bridgewater, NJ 08807